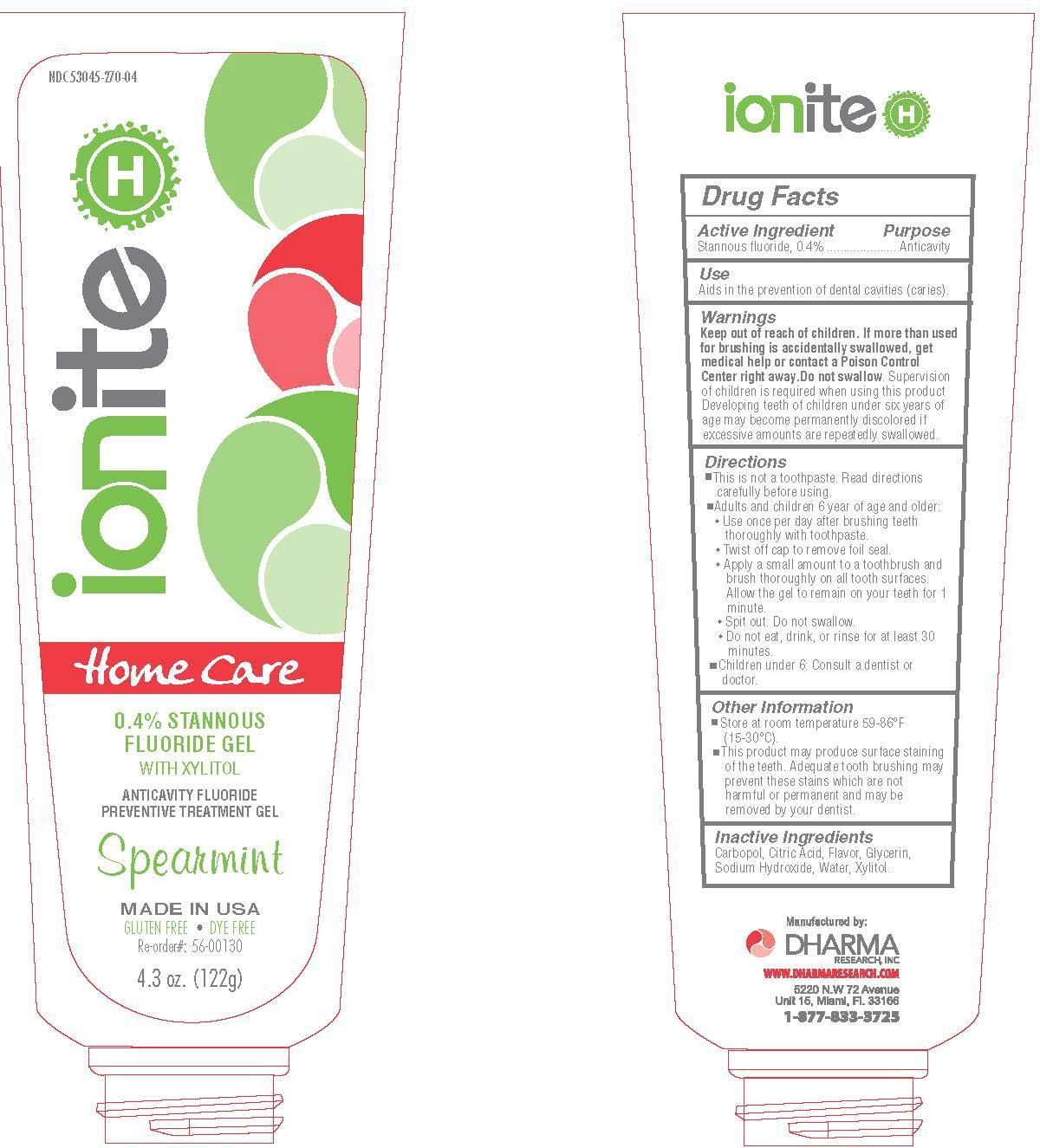 DRUG LABEL: Ionite H
NDC: 53045-270 | Form: GEL, DENTIFRICE
Manufacturer: Dharma Research, Inc.
Category: otc | Type: HUMAN OTC DRUG LABEL
Date: 20231011

ACTIVE INGREDIENTS: STANNOUS FLUORIDE 0.4 mg/100 g
INACTIVE INGREDIENTS: CARBOMER HOMOPOLYMER TYPE C (ALLYL PENTAERYTHRITOL CROSSLINKED); CITRIC ACID MONOHYDRATE; GLYCERIN; SODIUM HYDROXIDE; WATER; XYLITOL

Active Ingredient

Stannous fluoride, 0.4%

Purpose

Anticavity

Uses

Aids in the prevention of dental cavities (caries).

Warnings

Keep out of reach of children. If more than used for brushing is accidentally swallowed, get medical help or contact a Poison Control Center right away.

Do not swallow.

WARNINGS

Supervision of children is required when using this product. Developing teeth of children under six years of age may become permanently discolored if excessive amounts are repeatedly swallowed.

Directions

• This is not a toothpaste. Read directions carefully before using.
• Adults and children 6 years of age and older:
o Use once per day after brushing teeth thoroughly with toothpaste
o Twist off cap to remove foil seal
o Apply a small amount to a toothbrush and brush thoroughly on all tooth surfaces.
o Allow the gel to remain on your teeth for 1 minute
o Spit out. Do not swallow
o Do not eat, drink, or rinse for at least 30 minutes
• Children under 6: consult a dentist or doctor

Other Information

- Store at room temperature 59 – 86°F (15 – 30°C)
- This product may produce surface staining of the teeth. Adequate tooth brushing may prevent these stains which are not harmful or permanent and may be removed by your dentist

Inactive Ingredients

Carbopol, citric acid, flavor, glycerin, sodium hydroxide, water, xylitol

Manufactured by Dharma Research, Inc.

www.dharmaresearch.com

5220 N.W. 72 Avenue, Unit 15

Miami, FL 33166

1-877-833-3725

Ionite H

NDC 53045-270-04

Home Care

0.4% Stannous Fluoride Gel with Xylitol

Anticavity Fluoride Preventative Treatment Gel

Spearmint

Made in USA

Gluten Free Dye Free

Reorder#: 56-00130

4.3 oz. (122 g)